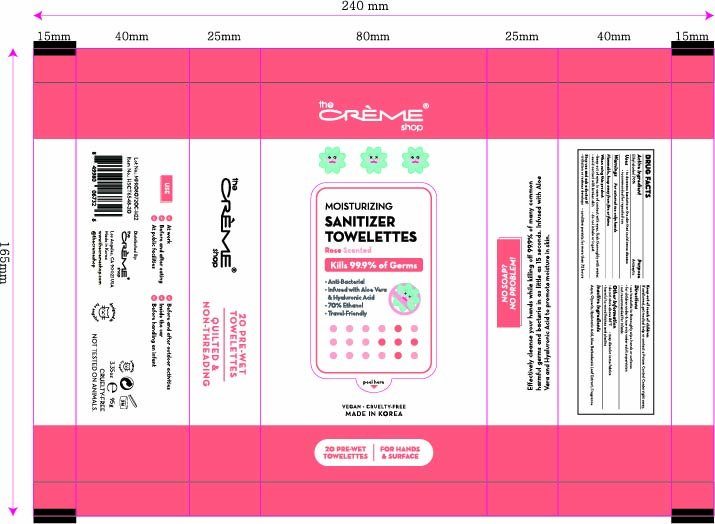 DRUG LABEL: The creme shop Moisturizing Sanitizer Towelettes Rose Scented
NDC: 74741-7201 | Form: CLOTH
Manufacturer: MPRBRAIN CO.LTD
Category: otc | Type: HUMAN OTC DRUG LABEL
Date: 20200722

ACTIVE INGREDIENTS: ALCOHOL 0.7 1/1 1
INACTIVE INGREDIENTS: ALOE VERA LEAF; GLYCERIN; HYALURONIC ACID; WATER

The creme shop Moisturizing Sanitizer Towelettes Rose Scented: 20 Towelettes
74741-7201-1